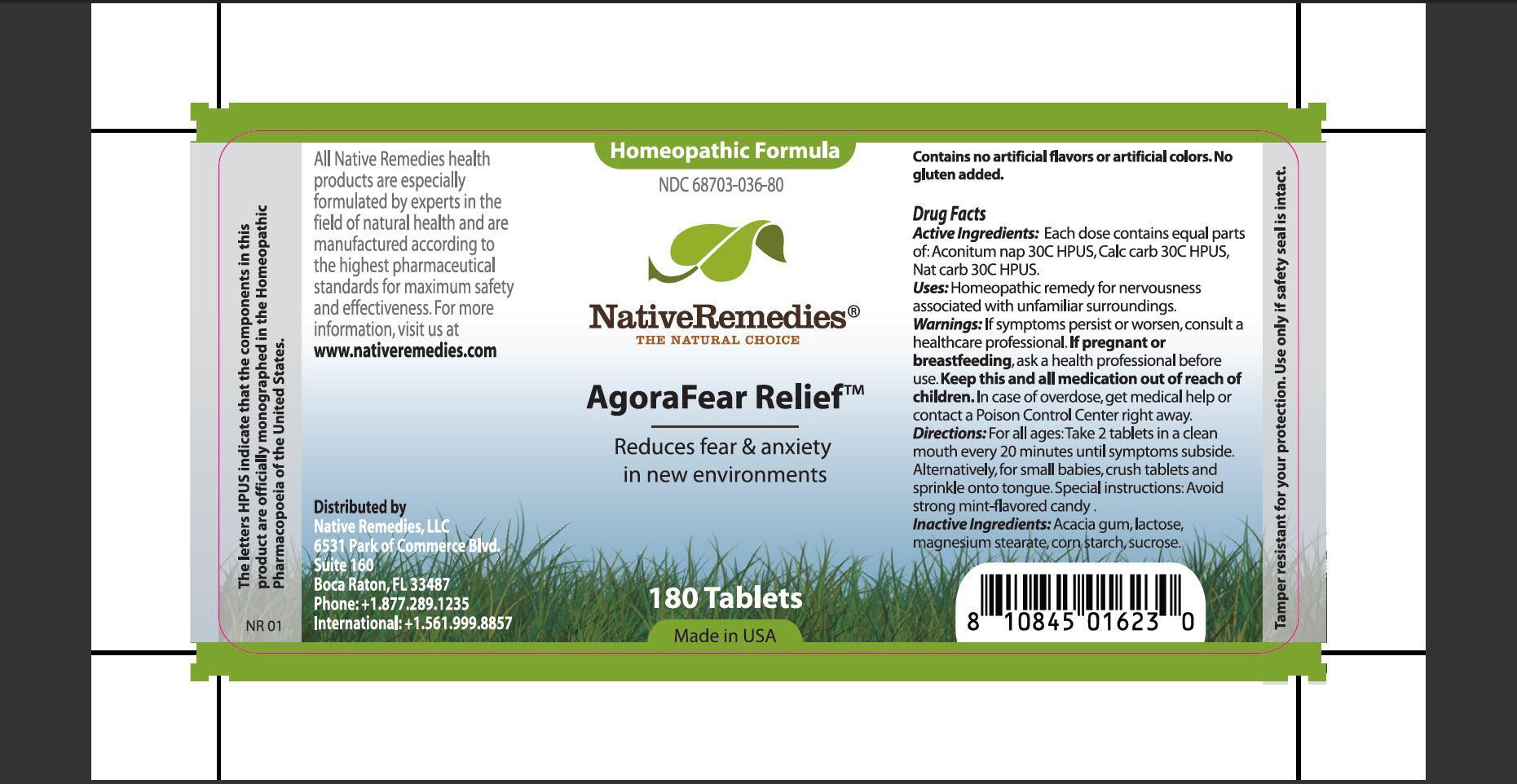 DRUG LABEL: AgoraFear Relief
NDC: 68703-036 | Form: TABLET
Manufacturer: Native Remedies, LLC
Category: homeopathic | Type: HUMAN OTC DRUG LABEL
Date: 20120906

ACTIVE INGREDIENTS: ACONITUM NAPELLUS 30 [hp_C]/1 1; OYSTER SHELL CALCIUM CARBONATE, CRUDE 30 [hp_C]/1 1; SODIUM CARBONATE 30 [hp_C]/1 1
INACTIVE INGREDIENTS: ACACIA; LACTOSE; MAGNESIUM STEARATE; STARCH, CORN; SUCROSE

AgoraFear Relief

PURPOSE

Reduces fear and anxiety in new environments

ACTIVE INGREDIENT

Active Ingredients: Each dose contains equal parts of: Aconitum nap 30C HPUS, Calc carb 30C HPUS, Nat carb 30C HPUS.

INDICATIONS AND USAGE

Uses: Homeopathic remedy for nervousness associated with unfamiliar surroundings.

WARNINGS

Warnings: If symptoms persist or worsen, consult a healthcare professional.

PREGNANCY OR BREAST FEEDING

If pregnant or breastfeeding, ask a health professional before use.

KEEP OUT OF REACH OF CHILDREN

Keep this and all medication out of reach of children.

OVERDOSAGE

In case of overdose, get medical help or contact a Poison Control Center right away.

DOSAGE AND ADMINISTRATION

Directions: For all ages: Take 2 tablets in a clean mouth every 20 minutes until symptoms subside. Alternatively, for small babies, crush tablets and sprinkle onto tongue. Special instructions: Avoid strong mint-flavored candy.

INACTIVE INGREDIENT

Inactive Ingredients: Acacia gum, lactose, magnesium stearate, corn starch, sucrose.

INFORMATION FOR OWNERS/CAREGIVERS

The letters HPUS indicate that the components in this product are officially monographed in the Homeopathic Pharmacopoeia of the United States.

All Native Remedies health products are especially formulated by experts in the field of natural health and are manufactured according to the highest pharmaceutical standards for maximum safety and effectiveness. For more information, visit us at www.nativeremedies.com

Distributed by
Native Remedies, LLC
6531 Park of Commerce Blvd.
Suite 160
Boca Raton, FL 33487
Phone: +1.877.289.1235
International: +1.561.999.8857

Contains no artificial flavors or artificial colors. No gluten added.

STORAGE AND HANDLING

Tamper resistant for your protection. Use only if safety seal is intact.